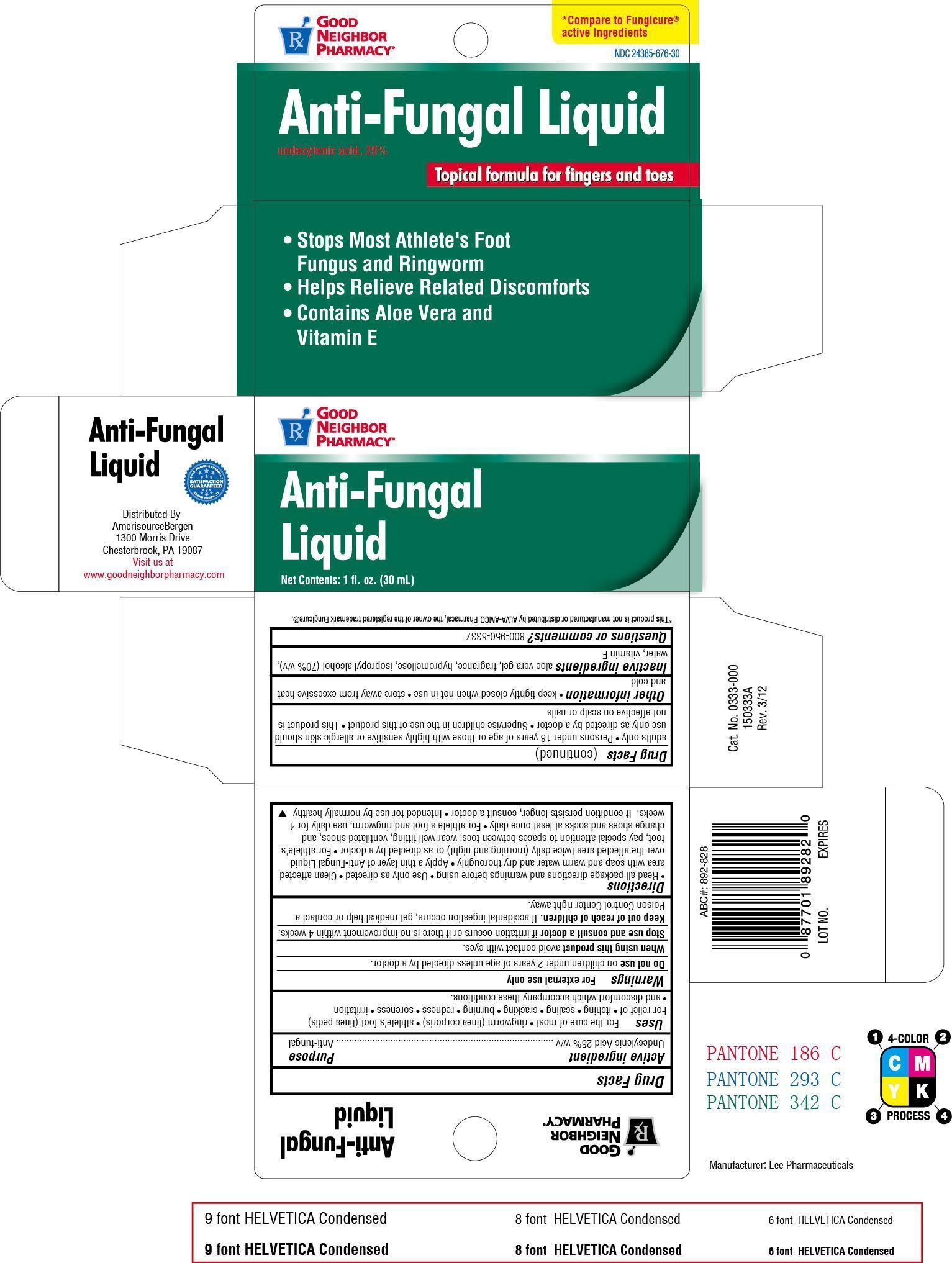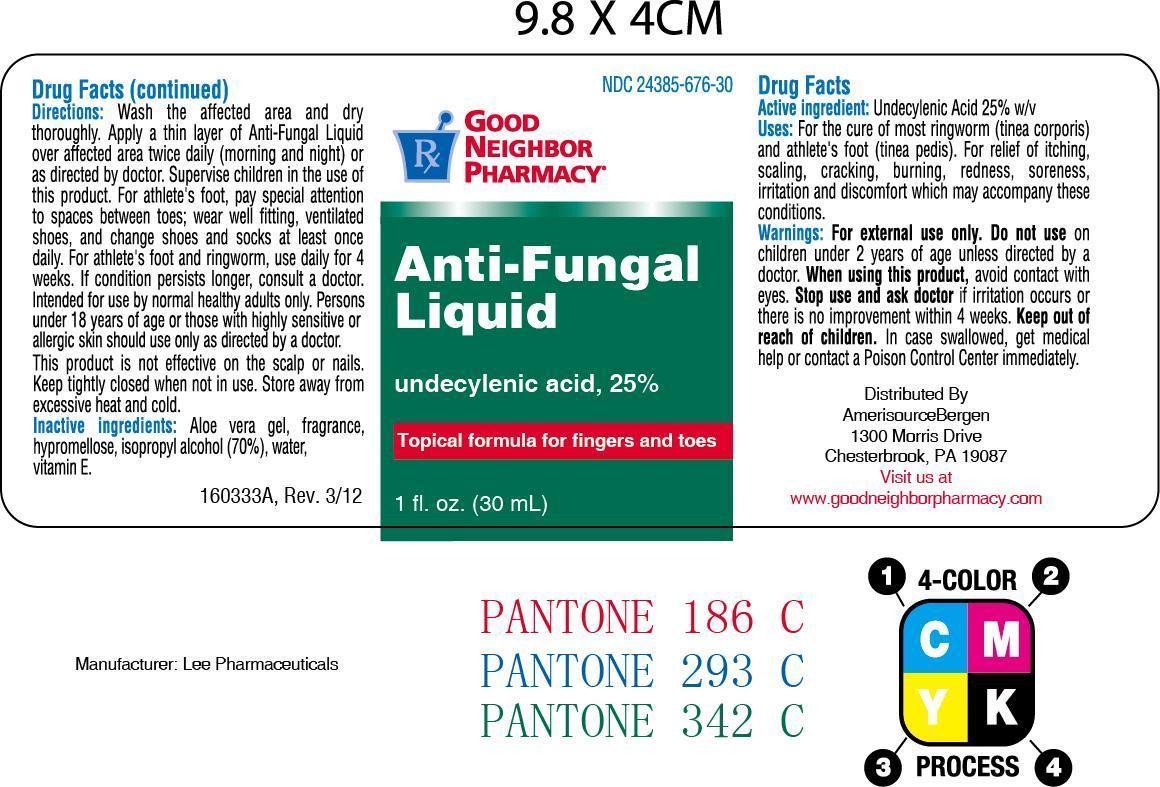 DRUG LABEL: Good Neighbor Anti-Fungal
NDC: 24385-676 | Form: LIQUID
Manufacturer: AmerisourceBergen Drug Corporation (Good Neighbor Pharmacy)
Category: otc | Type: HUMAN OTC DRUG LABEL
Date: 20130627

ACTIVE INGREDIENTS: UNDECYLENIC ACID 250 mg/1 mL
INACTIVE INGREDIENTS: ALOE VERA LEAF; HYPROMELLOSES; isopropyl alcohol; WATER; .ALPHA.-TOCOPHEROL ACETATE, D-

Drug Facts

Active ingredient

Undecylenic Acid, 25% w/v

Purpose

Anti-fungal

Uses

For the cure of most ringworm (tinea corporis) and athlete's Foot (tinea pedis). For relief of itching, scaling , cracking, burning, redness, soreness, irritation, and discomfort which accompany these conditions.

Warnings

For external use only

Do not use on children under 2 years of ae unless directed by a doctor.

When using this product avoid contact with eyes

Stop use and consult a doctor if irritation occurs or if there is no improvement within 4 weeks.

Keep out of reach of children. If accidental ingestion occurs, get medical help or contact a Poison Control Center right away.

Directions

- Read all package directions and warnings before using.
- Use only as directed.
- Clean affected area with soap and warm water and dry thoroughly.
- Apply a thin layer of Anti-Fungal Liquid over the affected area twice daily (morning and night) or as directed by a doctor.
- For athlete's foot, pay special attention to spaces between toes; wear well fitting, ventilated shoes, and change shoes and socks at least once daily
- For athlete's foot and ringworm, use daily for 4 weeks. If condition persists longer, consult a doctor.
- Intended for use by normally healthy adults only.
- Persons under 18 years of age or those with highly sensitive or allergic skin should use only as directed by a doctor.
- Supervise shildren in the use of this product
- This product is not effective on scalp or nails.

Other information

- keep thighly closed when not in use
- store away from excessive heat and cold

Inactive ingredients

aloe vera gel, fragrance, hypromellose, isopropyl alcohol (70% v/v), water, vitamin E